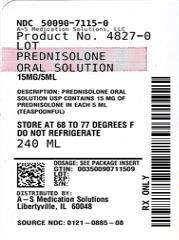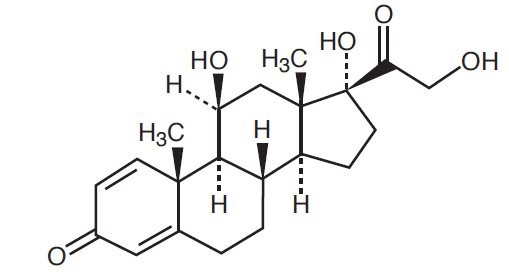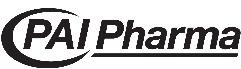 DRUG LABEL: Prednisolone
NDC: 50090-7115 | Form: SOLUTION
Manufacturer: A-S Medication Solutions
Category: prescription | Type: HUMAN PRESCRIPTION DRUG LABEL
Date: 20260123

ACTIVE INGREDIENTS: PREDNISOLONE 15 mg/5 mL
INACTIVE INGREDIENTS: BENZOIC ACID; DEHYDRATED ALCOHOL; ANHYDROUS CITRIC ACID; EDETATE DISODIUM; GLYCERIN; PROPYLENE GLYCOL; WATER; SODIUM SACCHARIN; SUCROSE; FD&C BLUE NO. 1; FD&C RED NO. 40

PrednisoLONE Oral Solution USP
15 mg/5 mL
Rx Only

DESCRIPTION

Prednisolone Oral Solution USP contains prednisolone which is a glucocorticoid. Glucocorticoids are adrenocortical steroids, both naturally occurring and synthetic, which are readily absorbed from the gastrointestinal tract.

Prednisolone is a white to practically white, odorless, crystalline powder. It is very slightly soluble in water, soluble in methanol and in dioxane; sparingly soluble in acetone and in alcohol; slightly soluble in chloroform.

The chemical name for prednisolone is Pregna-1,4-diene-3,20-dione,11,17,21-trihydroxy-,(11β)-.

C21H28O5 M.W. 360.45

Prednisolone Oral Solution USP, 15 mg/5 mL contains 15 mg of prednisolone in each 5 mL. Benzoic acid, 0.1% is added as a preservative. It also contains alcohol 5%, citric acid (anhydrous), edetate disodium, glycerin, propylene glycol, purified water, saccharin sodium, sucrose, FD&C blue #1 and FD&C red #40.

CLINICAL PHARMACOLOGY

Naturally occurring glucocorticoids (hydrocortisone and cortisone), which also have salt-retaining properties, are used as replacement therapy in adrenocortical deficiency states. Their synthetic analogs such as prednisolone are primarily used for their potent anti-inflammatory effects in disorders of many organ systems.

Glucocorticoids such as prednisolone cause profound and varied metabolic effects. In addition, they modify the body’s immune responses to diverse stimuli.

INDICATIONS AND USAGE

Prednisolone Oral Solution USP is indicated in the following conditions:

1. Endocrine Disorders

Primary or secondary adrenocortical insufficiency (hydrocortisone or cortisone is the first choice: synthetic analogs may be used in conjunction with mineralocorticoids where applicable: in infancy mineralocorticoid supplementation is of particular importance).

Congenital adrenal hyperplasia

Nonsuppurative thyroiditis

Hypercalcemia associated with cancer

2. Rheumatic Disorders

As adjunctive therapy for short-term administration (to tide the patient over an acute episode or exacerbation) in:

Psoriatic arthritis

Rheumatoid arthritis, including juvenile rheumatoid arthritis (selected cases may require low-dose maintenance therapy)

Ankylosing spondylitis

Acute and subacute bursitis

Acute nonspecific tenosynovitis

Acute gouty arthritis

Post-traumatic osteoarthritis

Synovitis of osteoarthritis

Epicondylitis

3. Collagen Diseases

During an exacerbation or as maintenance therapy in selected cases of:

Systemic lupus erythematosus

Acute rheumatic carditis

4. Dermatologic Diseases

Pemphigus

Bullous dermatitis herpetiformis

Severe erythema multiforme (Stevens-Johnson syndrome)

Exfoliative dermatitis

Mycosis fungoides

Severe psoriasis

Severe seborrheic dermatitis

5. Allergic States

Control of severe or incapacitating allergic conditions intractable to adequate trials of conventional treatment:

Seasonal or perennial allergic rhinitis

Bronchial asthma

Contact dermatitis

Atopic dermatitis

Serum sickness

Drug hypersensitivity reactions

6. Ophthalmic Diseases

Severe acute and chronic allergic and inflammatory processes involving the eye and its adnexa such as:

Allergic corneal marginal ulcers

Herpes zoster ophthalmicus

Anterior segment inflammation

Diffuse posterior uveitis and choroiditis

Sympathetic ophthalmia

Allergic conjunctivitis

Keratitis

Chorioretinitis

Optic neuritis

Iritis and Iridocyclitis

7. Respiratory Disorders

Symptomatic sarcoidosis

Loeffler’s syndrome not manageable by other means

Berylliosis

Fulminating or disseminated pulmonary tuberculosis when used concurrently with appropriate chemotherapy

Aspiration pneumonitis

8. Hematologic Disorders

Idiopathic thrombocytopenic purpura in adults

Secondary thrombocytopenia in adults

Acquired (autoimmune) hemolytic anemia

Erythroblastopenia (RBC anemia)

Congenital (erythroid) hypoplastic anemia

9. Neoplastic Diseases

For palliative management of:

Leukemias and lymphomas in adults

Acute leukemia of childhood

10. Edematous States

To induce a diuresis or remission of proteinuria in the nephrotic syndrome, without uremia, of the idiopathic type or that due to lupus erythematosus.

11. Gastrointestinal Diseases

To tide the patient over a critical period of the disease in:

Ulcerative colitis

Regional enteritis

12. Miscellaneous

Tuberculous meningitis with subarachnoid block or impending block used concurrently with appropriate antituberculous chemotherapy. Trichinosis with neurologic or myocardial involvement.

In addition to the above indications, Prednisolone Oral Solution USP is indicated for systemic dermatomyositis (polymyositis).

CONTRAINDICATIONS

Systemic fungal infections.

WARNINGS

In patients on corticosteroid therapy subjected to unusual stress, increased dosage of rapidly acting corticosteroids before, during, and after the stressful situation is indicated.

Immunosuppression and Increased Risk of Infection

Corticosteroids, including Prednisolone Oral Solution USP, suppress the immune system and increase the risk of infection with any pathogen, including viral, bacterial, fungal, protozoan, or helminthic pathogens. Corticosteroids can:

- Reduce resistance to new infections
- Exacerbate existing infections
- Increase the risk of disseminated infections
- Increase the risk of reactivation or exacerbation of latent infections
- Mask some signs of infection

Corticosteroid-associated infections can be mild but can be severe and at times fatal. The rate of infectious complications increases with increasing corticosteroid dosages.

Monitor for the development of infection and consider Prednisolone Oral Solution USP withdrawal or dosage reduction as needed.

Do not administer Prednisolone Oral Solution USP by an intraarticular, intrabursal, intratendinous, or intralesional route in the presence of acute local infection.

Tuberculosis

Prednisolone Oral Solution USP is used to treat a condition in patients with latent tuberculosis or tuberculin reactivity, reactivation of tuberculosis may occur. Closely monitor such patients for reactivation. During prolonged Prednisolone Oral Solution USP therapy, patients with latent tuberculosis or tuberculin reactivity should receive chemoprophylaxis.

Varicella Zoster and Measles Viral Infections

Varicella and measles can have a serious or even fatal course in non-immune patients taking corticosteroids, including Prednisolone Oral Solution USP. In corticosteroids-treated patients who have not had these diseases or are non-immune, particular care should be taken to avoid exposure to varicella and measles:

- If a Prednisolone Oral Solution USP-treated patient is exposed to varicella, prophylaxis with varicella zoster immune globulin may be indicated. If varicella develops, treatment with antiviral agents may be considered.
- If a Prednisolone Oral Solution USP-treated patient is exposed to measles, prophylaxis with immunoglobulin may be indicated.

Hepatitis B Virus Reactivation

Hepatitis B Virus reactivation can occur in patients who are hepatitis B carriers treated with immunosuppressive dosages of corticosteroids, including Prednisolone Oral Solution USP. Reactivation can also occur infrequently in corticosteroid-treated patients who appear to have resolved hepatitis B infection.

Screen patients for hepatitis B infection before initiating immunosuppressive (e.g., prolonged) treatment with Prednisolone Oral Solution USP. For patients who show evidence of hepatitis B infection, recommend consultation with physicians with expertise in managing hepatitis B regarding and consideration for hepatitis B antiviral therapy.

Fungal Infections

Corticosteroids, including Prednisolone Oral Solution USP, may exacerbate systemic fungal infections; therefore, avoid Prednisolone Oral Solution USP use in the presence of such infections unless Prednisolone Oral Solution USP is needed to control drug reactions. For patients on chronic Prednisolone Oral Solution USP therapy who develop systemic fungal infections, Prednisolone Oral Solution USP withdrawal or dosage reduction is recommended.

Amebiasis

Corticosteroids, including Prednisolone Oral Solution USP, may activate latent amebiasis. Therefore, it is recommended that latent amebiasis or active amebiasis be ruled out before initiating Prednisolone Oral Solution USP in patients who have spent time in the tropics or patients with unexplained diarrhea.

Strongyloides Infestation

Corticosteroids, including Prednisolone Oral Solution USP, should be used with great care in patients with known or suspected Strongyloides (threadworm) infestation. In such patients, corticosteroid-induced immunosuppression may lead to Strongyloides hyperinfection and dissemination with widespread larval migration, often accompanied by severe enterocolitis and potentially fatal gram-negative septicemia.

Cerebral Malaria

Avoid corticosteroids, including Prednisolone Oral Solution USP, in patients with cerebral malaria.

Kaposi’s Sarcoma

Kaposi’s sarcoma has been reported to occur in patients receiving corticosteroid therapy, most often for chronic conditions. Discontinuation of corticosteroids may result in clinical improvement of Kaposi’s sarcoma.

Prolonged use of corticosteroids may produce posterior subcapsular cataracts, glaucoma with possible damage to the optic nerves, and may enhance the establishment of secondary ocular infections due to fungi or viruses.

Average and large doses of hydrocortisone or cortisone can cause elevation of blood pressure, salt and water retention, and increased excretion of potassium. These effects are less likely to occur with the synthetic derivatives except when used in large doses. Dietary salt restriction and potassium supplementation may be necessary. All corticosteroids increase calcium excretion.

While on corticosteroid therapy, patients should not be vaccinated against smallpox. Other immunization procedures should not be undertaken in patients who are on corticosteroids, especially on high dose, because of possible hazards of neurological complications and a lack of antibody response.

Use in Pregnancy: Since adequate human reproduction studies have not been done with corticosteroids, the use of these drugs in pregnancy, nursing mothers, or women of childbearing potential requires that the possible benefits of the drug be weighed against the potential hazards to the mother and embryo or fetus. Infants born of mothers who have received substantial doses of corticosteroids during pregnancy should be carefully observed for signs of hypoadrenalism.

PRECAUTIONS

General:

Drug-induced secondary adrenocortical insufficiency may be minimized by gradual reduction of dosage. This type of relative insufficiency may persist for months after discontinuation of therapy; therefore, in any situation of stress occurring during that period, hormone therapy should be reinstituted.

Since mineralocorticoid secretion may be impaired, salt and/or a mineralocorticoid should be administered concurrently.

There is an enhanced effect of corticosteroids on patients with hypothyroidism and in those with cirrhosis.

Corticosteroids should be used cautiously in patients with ocular herpes simplex because of possible corneal perforation.

The lowest possible dose of corticosteroid should be used to control the condition under treatment, and when reduction in dosage is possible, the reduction should be gradual.

Psychic derangements may appear when corticosteroids are used, ranging from euphoria, insomnia, mood swings, personality changes, and severe depression, to frank psychotic manifestations. Also, existing emotional instability or psychotic tendencies may be aggravated by corticosteroids. Aspirin should be used cautiously in conjunction with corticosteroids in hypoprothrombinemia. Steroids should be used with caution in nonspecific ulcerative colitis if there is a probability of impending perforation, abscess or other pyogenic infections; diverticulitis; fresh intestinal anastomoses; active or latent peptic ulcer; renal insufficiency; hypertension; osteoporosis; and myasthenia gravis. Growth and development of infants and children on prolonged corticosteroid therapy should be carefully observed.

Information for Patients:

Patients who are on immunosuppressant doses of corticosteroids should be warned to avoid exposure to chickenpox or measles. Patients should also be advised that if they are exposed, medical advice should be sought without delay.

ADVERSE REACTIONS

Fluid and Electrolyte Disturbances

Sodium retention

Fluid retention

Congestive heart failure in susceptible patients

Potassium loss

Hypokalemic alkalosis

Hypertension

Musculoskeletal

Muscle weakness

Steroid myopathy

Loss of muscle mass

Osteoporosis

Vertebral compression fractures

Aseptic necrosis of femoral and humeral heads

Pathologic fracture of long bones

Gastrointestinal

Peptic ulcer with possible perforation and hemorrhage

Pancreatitis

Abdominal distention

Ulcerative esophagitis

Dermatologic

Impaired wound healing

Thin fragile skin

Petechiae and ecchymoses

Facial erythema

Increased sweating

May suppress reactions to skin tests

Neurological

Convulsions

Increased intracranial pressure with papilledema (pseudo-tumor cerebri) usually after

treatment

Vertigo

Headache

Endocrine

Menstrual irregularities

Development of Cushingoid state

Suppression of growth in pediatric patients

Secondary adrenocortical and pituitary unresponsiveness, particularly in times of stress, as in

trauma, surgery, or illness

Decreased carbohydrate tolerance

Manifestations of latent diabetes mellitus

Increased requirements for insulin or oral hypoglycemic agents in diabetics

Ophthalmic

Posterior subcapsular cataracts

Increased intraocular pressure

Glaucoma

Exophthalmos

Metabolic

Negative nitrogen balance due to protein catabolism

To report SUSPECTED ADVERSE REACTIONS, contact PAI Pharma at 1-800-845-8210 or FDA at 1-800-FDA-1088 or www.fda.gov/medwatch.

DOSAGE AND ADMINISTRATION

Dosage of prednisolone oral solution should be individualized according to the severity of the disease and the response of the patient. For infants and children, the recommended dosage should be governed by the same considerations rather than strict adherence to the ratio indicated by age or body weight.

Hormone therapy is an adjunct to and not a replacement for conventional therapy. Dosage should be decreased or discontinued gradually when the drug has been administered for more than a few days.

The severity, prognosis, expected duration of the disease, and the reaction of the patient to medication are primary factors in determining dosage. If a period of spontaneous remission occurs in a chronic condition, treatment should be discontinued.

Blood pressure, body weight, routine laboratory studies, including two-hour postprandial blood glucose and serum potassium, and a chest X-ray should be obtained at regular intervals during prolonged therapy. Upper GI X-rays are desirable in patients with known or suspected peptic ulcer disease.

The initial dosage of prednisolone oral solution may vary from 5 mg to 60 mg per day depending on the specific disease entity being treated. In situations of less severity, lower doses will generally suffice while in selected patients higher initial doses may be required. The initial dosage should be maintained or adjusted until a satisfactory response is noted. If after a reasonable period of time there is a lack of satisfactory clinical response, prednisolone oral solution should be discontinued and the patient transferred to other appropriate therapy. IT SHOULD BE EMPHASIZED THAT DOSAGE REQUIREMENTS ARE VARIABLE AND MUST BE INDIVIDUALIZED ON THE BASIS OF THE DISEASE UNDER TREATMENT AND THE RESPONSE OF THE PATIENT.

After a favorable response is noted, the proper maintenance dosage should be determined by decreasing the initial drug dosage in small decrements at appropriate time intervals until the lowest dosage which will maintain an adequate clinical response is reached. It should be kept in mind that constant monitoring is needed in regard to drug dosage. Included in the situations which may make dosage adjustments necessary are changes in clinical status secondary to remissions or exacerbations in the disease process, the patient’s individual drug responsiveness, and the effect of patient exposure to stressful situations not directly related to the disease entity under treatment. In this latter situation it may be necessary to increase the dosage of prednisolone oral solution for a period of time consistent with the patient’s condition. If after long-term therapy the drug is to be stopped, it is recommended that it be withdrawn gradually rather than abruptly.

HOW SUPPLIED

Product: 50090-7115

NDC: 50090-7115-0 120 mL in a BOTTLE, DISPENSING / 2 in a BOTTLE

NDC: 50090-7115-1 60 mL in a BOTTLE, DISPENSING / 4 in a BOTTLE

Manufactured by:

Greenville, SC 29605

R02/24